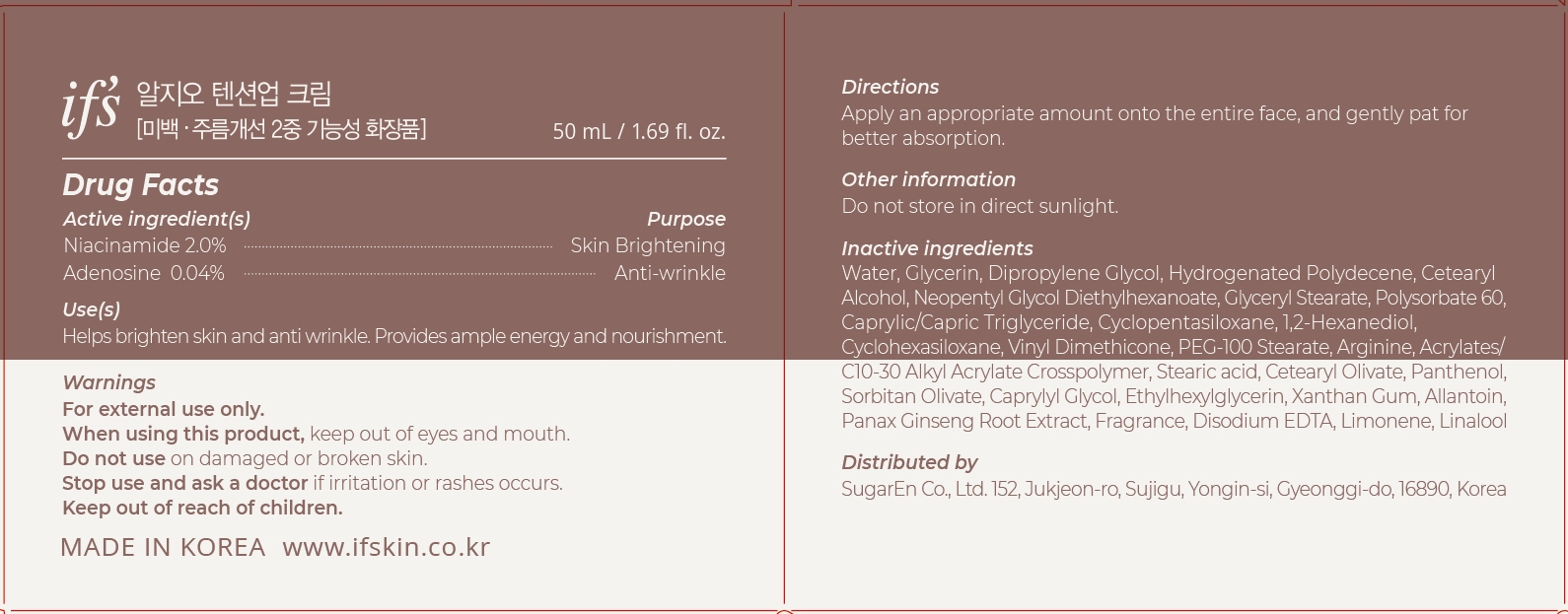 DRUG LABEL: RGO TENSION UPCREAM
NDC: 81897-503 | Form: CREAM
Manufacturer: SugarEn Co., Ltd.
Category: otc | Type: HUMAN OTC DRUG LABEL
Date: 20210529

ACTIVE INGREDIENTS: NIACINAMIDE 2 mg/100 mL; ADENOSINE 0.04 mg/100 mL
INACTIVE INGREDIENTS: GLYCERIN; CETOSTEARYL ALCOHOL; NEOPENTYL GLYCOL DIETHYLHEXANOATE; GLYCERYL MONOSTEARATE; 1,2-HEXANEDIOL; PEG-100 STEARATE; CAPRYLYL GLYCOL; ALLANTOIN; EDETATE DISODIUM ANHYDROUS; LIMONENE, (+)-; CYCLOMETHICONE 6; VINYL DIMETHICONE/METHICONE SILSESQUIOXANE CROSSPOLYMER; CETEARYL OLIVATE; PANTHENOL; POLYSORBATE 60; MEDIUM-CHAIN TRIGLYCERIDES; CYCLOMETHICONE 5; ARGININE; STEARIC ACID; SORBITAN OLIVATE; ETHYLHEXYLGLYCERIN; XANTHAN GUM; ASIAN GINSENG; WATER; DIPROPYLENE GLYCOL; LINALOOL, (+/-)-

81897-503 RGO TENSION UP CREAM

Active ingredient(s)

Niacinamide 2.0%

Adenosine 0.04%

Purpose

Skin Brightening, Anti-wrinkle

Use(s)

Helps brighten skin and anti wrinkle.

Provides ample energy and nourishment.

Warnings

For external only.

When using this product,

keep out of eyes and mouth.

Do not use

on damaged or broken skin.

Stop use and ask a doctor

if irritation or rashes occurs.

Keep out of reach of children.

Other information

Do not store in direct sunlight.

Directions

Apply an appropriate amount onto the entire face, and gently pat for better absorption.

Inactive indredients

Water, Glycerin, Dipropylene Glycol, Hydrogenated Polydecene, Cetearyl Alcohol, Neopentyl Glycol Diethylhexanoate, Glyceryl Stearate, Polysorbate 60, Caprylic/Capric Triglyceride, Cyclopentasiloxane, 1,2-Hexanediol, Cyclohexasiloxane, Vinyl Dimethicone, PEG-100 Stearate, Arginine, Acrylates/C10-30 Alkyl Acrylate Crosspolymer, Stearic acid, Cetearyl Olivate, Panthenol, Sorbitan Olivate, Caprylyl Glycol, Ethylhexylglycerin, Xanthan Gum, Allantoin, Panax Ginseng Root Extract, Fragrance, Disodium EDTA, Limonene, Linalool